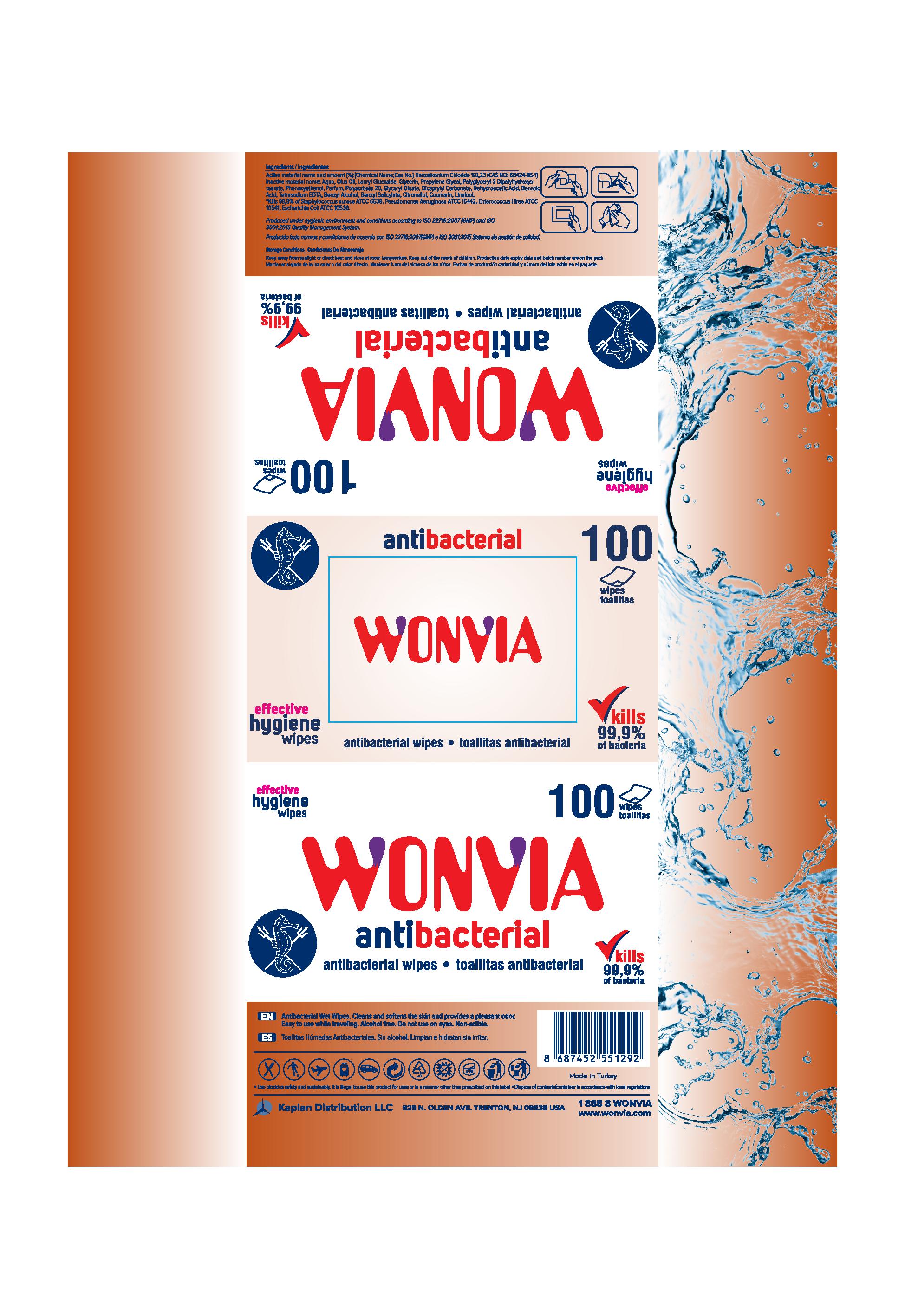 DRUG LABEL: Wonvia Antibacterial Wipes
NDC: 78876-707 | Form: CLOTH
Manufacturer: KAPLAN DISTRIBUTION LLC
Category: otc | Type: HUMAN OTC DRUG LABEL
Date: 20200806

ACTIVE INGREDIENTS: BENZALKONIUM CHLORIDE 0.23 g/100 g
INACTIVE INGREDIENTS: PHENOXYETHANOL; DICAPRYLYL CARBONATE; WATER; .BETA.-CITRONELLOL, (R)-; LAURYL GLUCOSIDE; GLYCERYL OLEATE; POLYSORBATE 20; EDETATE SODIUM; BENZYL SALICYLATE; GLYCERIN; DEHYDROACETIC ACID; PROPYLENE GLYCOL; BENZYL ALCOHOL; COUMARIN; POLYGLYCERYL-2 DIPOLYHYDROXYSTEARATE; BENZOIC ACID; LINALOOL, (+)-

DESCRIPTION

Wonvia Antibacterial Wipes

Active Ingredient(s)

Active material name and amount (%): (Chemical NAme; CAS No.) Benzalkonium Chloride %0,23 (CAS NO: 68424-85-1)

Inactive ingredients

Inactive material name: Aqua, Olus Oil, Lauryl Glucoside, Glycerin, Propylene Glycol, Polyglyceryl-2 Dipolyhydroxystearate, Phenoxyethanol, Parfum, Polysorbate 20, Glyceryl Oleate, Dicaprylyl Carbonate, Dehdroacetic Acid, Benzoic Acid, Tetrasodium EDTA, Benzyl Alcohol, Benzyl Salicylate, Citronellol, Coumarin, Linalool.

Purpose

Antibacterial Wet Wipes.

DOSAGE AND ADMINISTRATION

It is illegal to use this product for uses or in a manner other than prescribed on this label.

Use

Antibacterial Wet Wipes. Cleans and softens the skin and provides a pleasant odor.

Warnings

Non-edible.

Do not use on the eyes.

STORAGE AND HANDLING

Keep away from sunlight or direct heat and store at room temperature.

Keep out of reach of children.

DISPOSAL AND WASTE HANDLING

Dispose of contents/container in accordance with local regulations.

QUESTIONS

1 888 8 WONVIA

www.wonvia.com

Package label-Principal Display Panel

WONVIA antibacterial

antibacterial wipes

kills 99.9% of bacteria

100 wipes

effective hygiene wipes

use biocides safely and sustainably

production date, expiry date, and batch number are on the pack.

Kaplan Distribution LLC

828 N. Olden Ave., Trenton, NJ 08638 USA

Made in Turkey